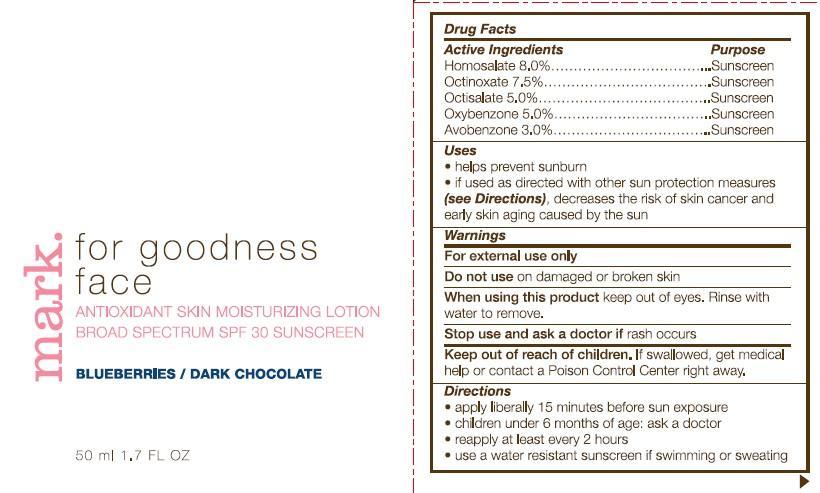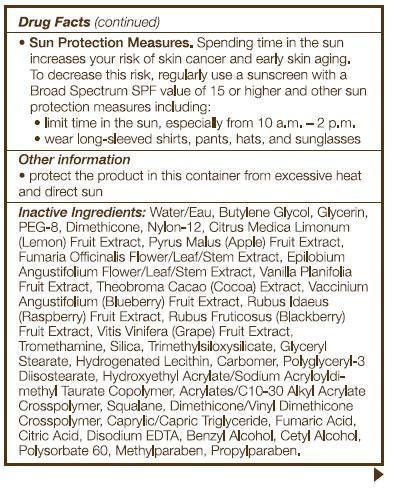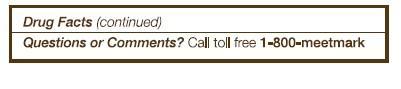 DRUG LABEL: mark. For Gooness Face
NDC: 10096-0144 | Form: LOTION
Manufacturer: Avon Products, Inc.
Category: otc | Type: HUMAN OTC DRUG LABEL
Date: 20130308

ACTIVE INGREDIENTS: HOMOSALATE 80 mg/1 mL; OCTINOXATE 75 mg/1 mL; OCTISALATE 50 mg/1 mL; OXYBENZONE 50 mg/1 mL; AVOBENZONE 30 mg/1 mL

Active Ingredients

Homosalate 8.0%.........

Octinoxate 7.5%...........

Octisalate 5.0%............

Oxybenzone 5.0%..........

Avobenzone 3.0%..........

Purpose

...........Sunscreen

...........Sunscreen

...........Sunscreen

...........Sunscreen

...........Sunscreen

Uses

- helps prevent sunburn
- if used as directed with other sun protection measures (see Directions), decreases the risk of skin cancer and early skin aging caused by the sun

Warnings

For external use only

Do not use on damaged or broken skin

When using this product keep out of eyes. Rinse with water to remove.

Stop use and ask a doctor if rash occurs

Keep out of reach of children. If swallowed, get medical help or contact a Poison Control Center right away.

Directions

- apply liberally 15 minutes before sun exposure
- children under 6 months of age: ask a doctor
- reapply at least every 2 hours
- use a water resistant sunscreen if swimming or sweating
- Sun Protection Measures. Spending time in the sun increases your risk of skin cancer and early skin aging. To decrease this risk, regularly use a sunscreen with a Broad Spectrum SPF value of 15 or higher and other sun protection measures including:
- limit time in the sun, especially from 10 a.m.-2 p.m.
- wear long-sleeved shirts, pants, hats, and sunglasses

Other information

- protect the product in this container from excessive heat and direct sun

INACTIVE INGREDIENT

Inactive Ingredients: Water/Eau, Butylene Glycol, Glycerin, PEG-8, Dimethicone, Nylon-12, Citrus Medica Limonum (Lemon) Fruit Extract, Pyrus Malus (Apple) Fruit Extract, Fumaria Officinalis Flower/Leaf/Stem Extract, Epilobium Angustifolium Flower/Leaf/Stem Extract, Vanilla Planifolia Fruit Extract, Theobroma Cacao (Cocoa) Extract, Vaccinium Angustifolium (Blueberry) Fruit Extract, Rubus Idaeus (Raspberry) Fruit Extract, Rubus Fruticosus (Blackberry) Fruit Extract, Vitis Vinifera (Grape) Fruit Extract, Tromethamine, Silica, Trimethylsiloxysilicate, Glyceryl Stearate, Hydrogenated Lecithin, Carbomer, Polyglyceryl-3 Diisostearate, Hydroxyethyl Acrylate/Sodium Acryloyldimethyl Taurate Copolymer, Acrylates/C10-30 Alkyl Acrylate Crosspolymer, Squalane, Dimethicone/Vinyl Dimethicone Crosspolymer, Caprylic/Capric Triglyceride, Fumaric Acid, Citric Acid, Disodium EDTA, Benzyl Alcohol, Cetyl Alcohol, Polysorbate 60, Methylparaben, Propylparaben

Questions or Comments? Call toll free 1-800-meetmark